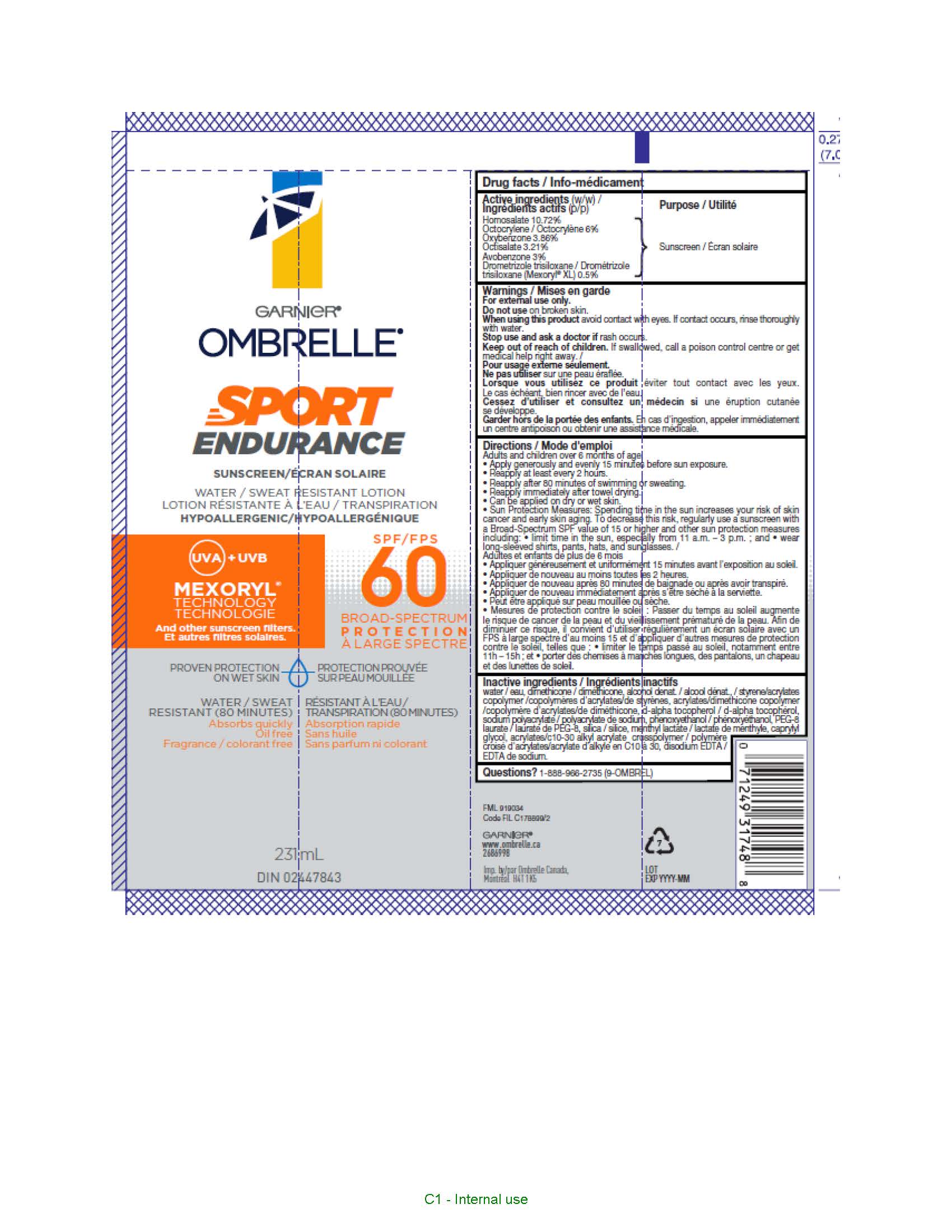 DRUG LABEL: Garnier Ombrelle Sport Endurance 60
NDC: 49967-488 | Form: LOTION
Manufacturer: L'OREAL USA PRODUCTS INC
Category: otc | Type: HUMAN OTC DRUG LABEL
Date: 20260107

ACTIVE INGREDIENTS: AVOBENZONE 30 mg/1 mL; DROMETRIZOLE TRISILOXANE 5 mg/1 mL; HOMOSALATE 107.2 mg/1 mL; OCTISALATE 32.1 mg/1 mL; OCTOCRYLENE 60 mg/1 mL; OXYBENZONE 38.6 mg/1 mL
INACTIVE INGREDIENTS: WATER; DIMETHICONE; ALCOHOL; STYRENE/ACRYLAMIDE COPOLYMER (500000 MW); TOCOPHEROL; SODIUM POLYACRYLATE (2500000 MW); PHENOXYETHANOL; PEG-8 LAURATE; SILICON DIOXIDE; MENTHYL LACTATE, (-)-; CAPRYLYL GLYCOL; CARBOMER INTERPOLYMER TYPE A (ALLYL SUCROSE CROSSLINKED); EDETATE DISODIUM

Drug Facts

Active ingredients

Avobenzone 3%

Drometrizole trisiloxane 0.5%

Homosalate 10.72%

Octisalate 3.21%

Octocrylene 6%

Oxybenzone 3.86%

Warnings

For external use only. When using this product avoid contact with eyes. If contact occurs, rinse thoroughlly with water. Do not use on broken skin. Stop use and ask a doctor if rash occurs. Keep out of reach of children. If swallowed get medical help or contact a poison control center right away.

Directions

Adults and children over 6 months and up. Apply generously and evenly 15 minutes before sun exposure. Reapply at least every 2 hours, after 80 minutes of swimming or sweating and immediately after towel drying. Can be applied on dry or wet skin. Sun Protection Measures. Spending time in the sun increases your risk of skin cancer and early skin aging. To decrease this risk regularly use a sunscreen with a broad spectrum SPF value of 15 or higher and other sun protection measure including limit time in the sun 11 a.m - 3 p.m and wear long sleeve shirts, pants, hats and sunglasses.

Inactive ingredients

water, dimethicone, alcohol denat., styrene/acrylates copolymer, acrylates/dimethicone copolymer, tocopherol, sodium polyacrylate, phenoxyethanol, PEG-8 laurate, silica, menthyl lactate, caprylyl glycol, acrylates/c10-30 alkyl acrylate crosspolymer, disodium EDTA